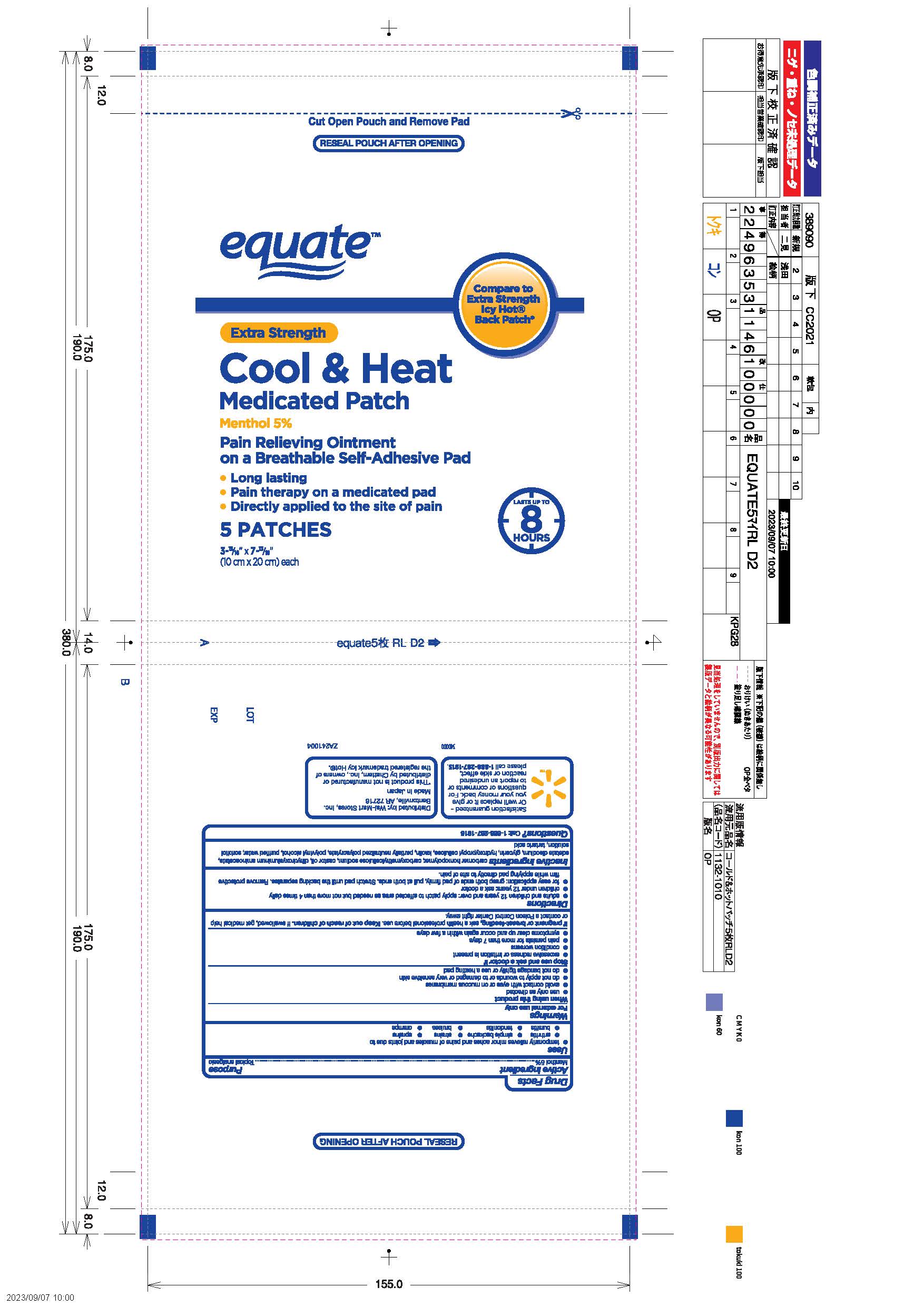 DRUG LABEL: Equate Cool and Heat
NDC: 49035-888 | Form: PATCH
Manufacturer: Wal-Mart Stores Inc
Category: otc | Type: HUMAN OTC DRUG LABEL
Date: 20250609

ACTIVE INGREDIENTS: MENTHOL, UNSPECIFIED FORM 50 mg/1 1
INACTIVE INGREDIENTS: CARBOMER HOMOPOLYMER TYPE B (ALLYL PENTAERYTHRITOL CROSSLINKED); CARBOXYMETHYLCELLULOSE SODIUM, UNSPECIFIED FORM; CASTOR OIL; DIHYDROXYALUMINUM AMINOACETATE; EDETATE DISODIUM; GLYCERIN; ISOPROPYL MYRISTATE; POLYVINYL ALCOHOL, UNSPECIFIED; POLYACRYLIC ACID (250000 MW); WATER; SORBITOL; TARTARIC ACID; HYDROXYPROPYL CELLULOSE (70000 WAMW)

Drug Facts - Equate Cool and Heat Extra Strength Medicated Patch

Active ingredient

Menthol 5%

Purpose

Menthol - Topical analgesic

Uses

temporarily relieves minor aches and pains of muscles and joints due to

- arthritis
- simple backache
- strains
- sprains
- bursitis
- tendonitis
- bruises
- cramps

Warnings

For external use only

When using this product

- use only as directed
- avoid contact with eyes or on mucous membranes
- do not apply to wounds or to damaged or very sensitive skin
- do not bandage tightly or use a heating pad

Stop use and ask a doctor if

- excessive redness or irritation is present
- condition worsens
- pain persists for more than 7 days
- symptoms clear up and occur again within a few days

If pregnant or breast-feeding,

ask a health professional before use.

Keep out of reach of children.

If swallowed, get medical help or contact a Poison Control Center right away.

Directions

- adults and children 12 years and over: apply patch to affected area as needed but no more than 4 times daily
- children under 12 years: ask a doctor
- for easy application: grasp both ends of pad firmly, pull at both ends. Stretch pad until the backing separates. Remove protective film while applying pad directly to site of pain.

Inactive ingredients

carbomer homopolymer, carboxymethylcellulose sodium, castor oil, dihydroxyaluminum aminoacetate, edetate disodium, glycerin, hydroxypropyl cellulose, kaolin, partially neutralized polycrylate, polyvinyl alcohol, purified water, sorbitol solution, tartaric acid

Questions?

Call: 1-888-287-1915